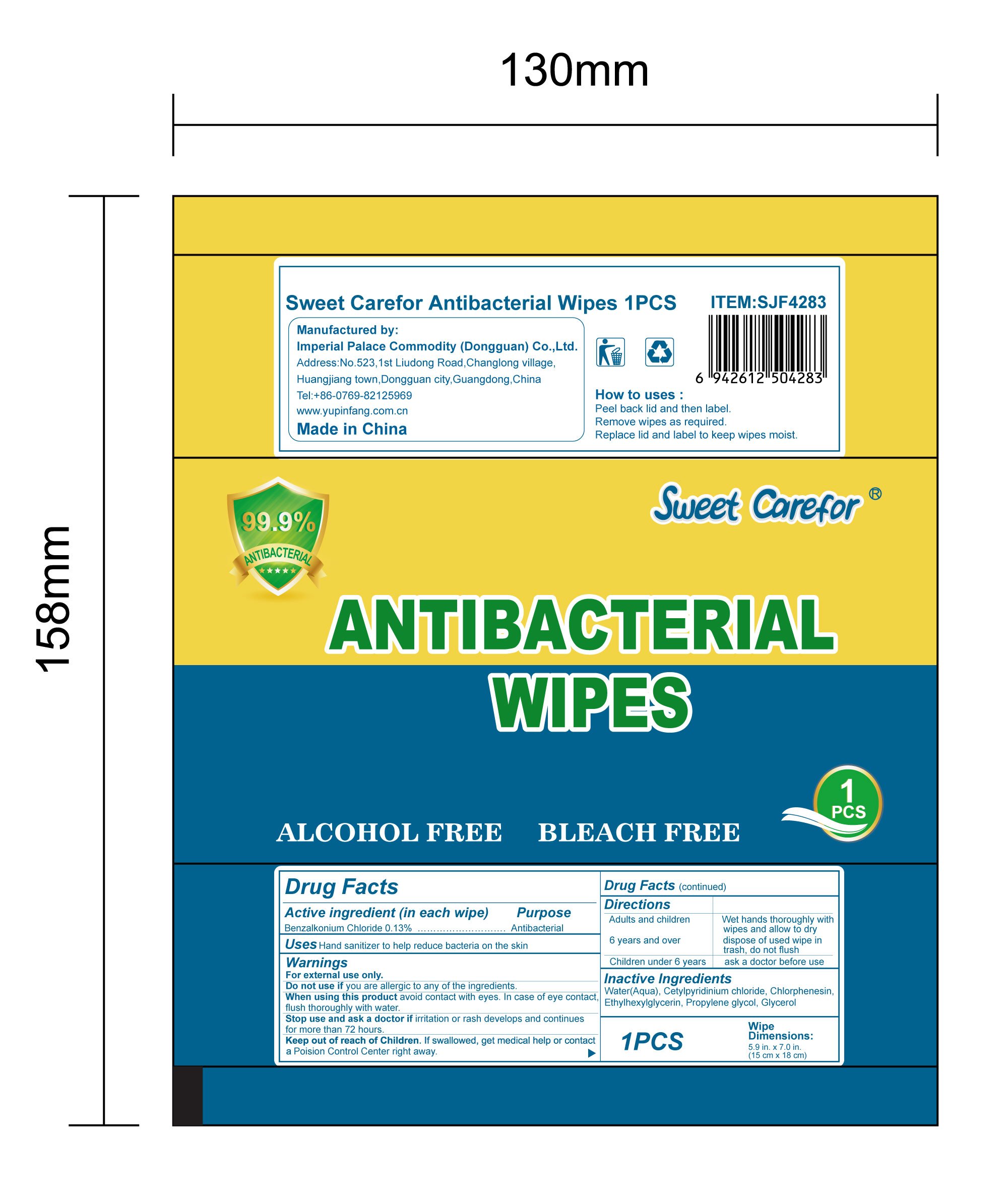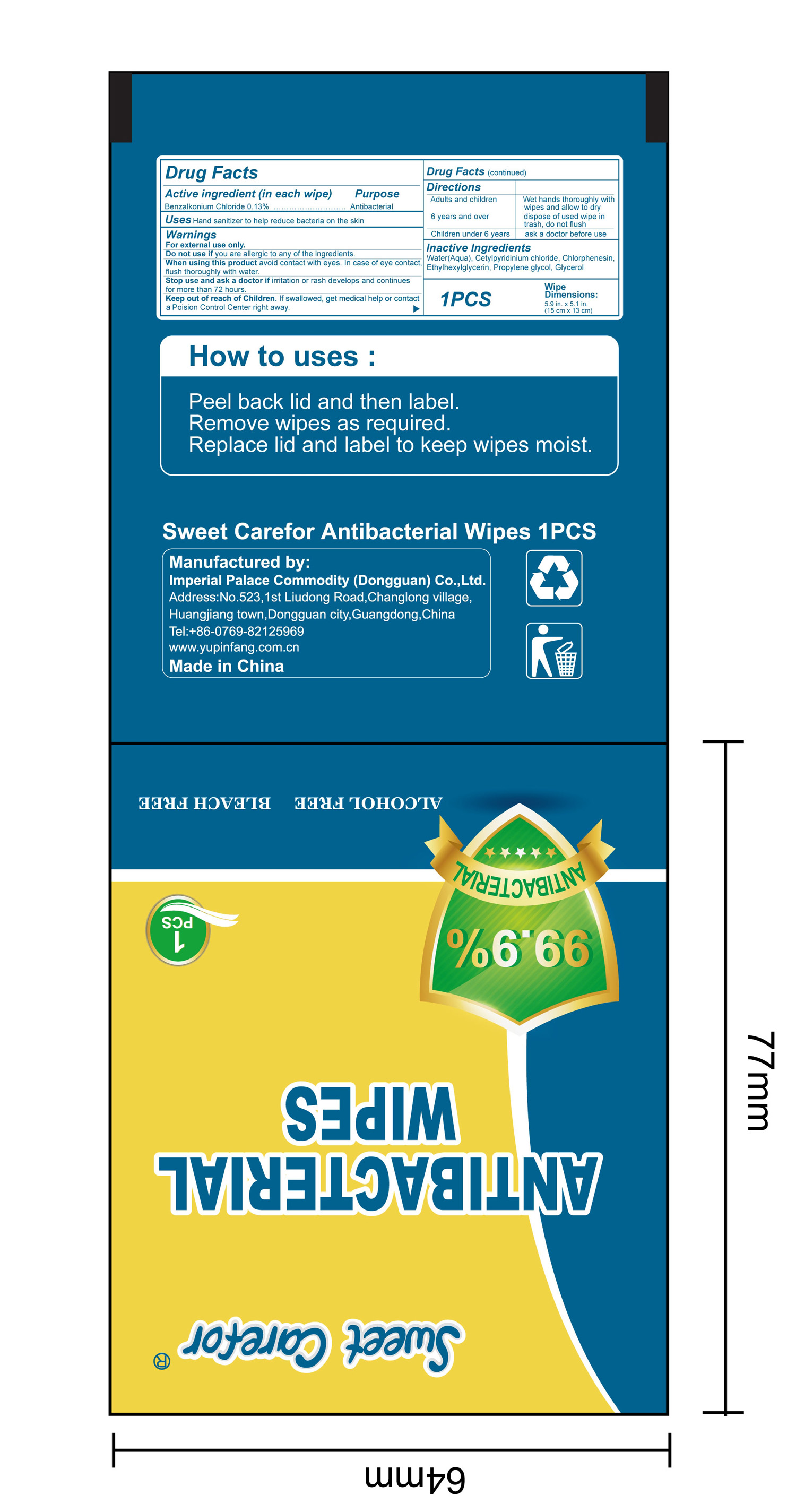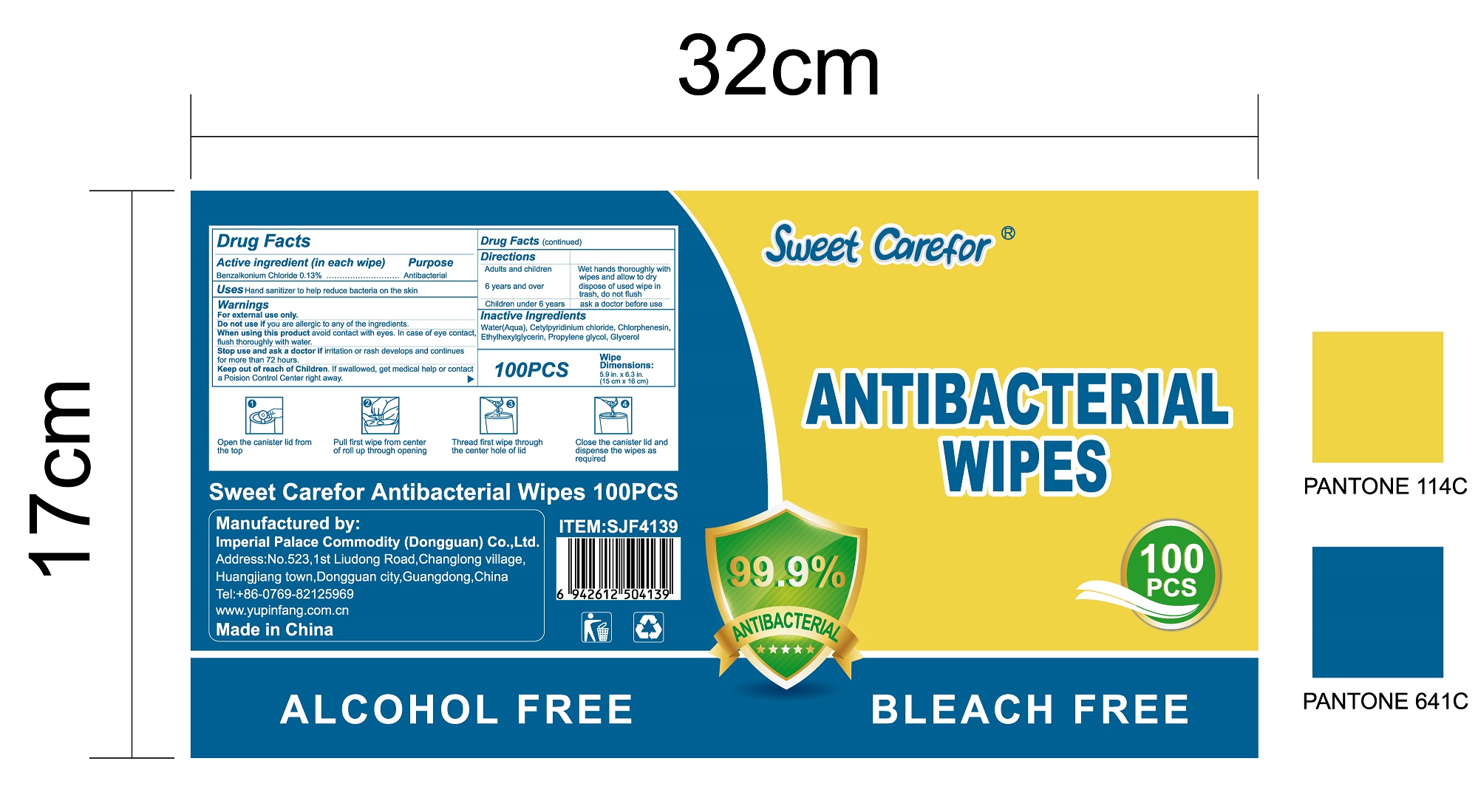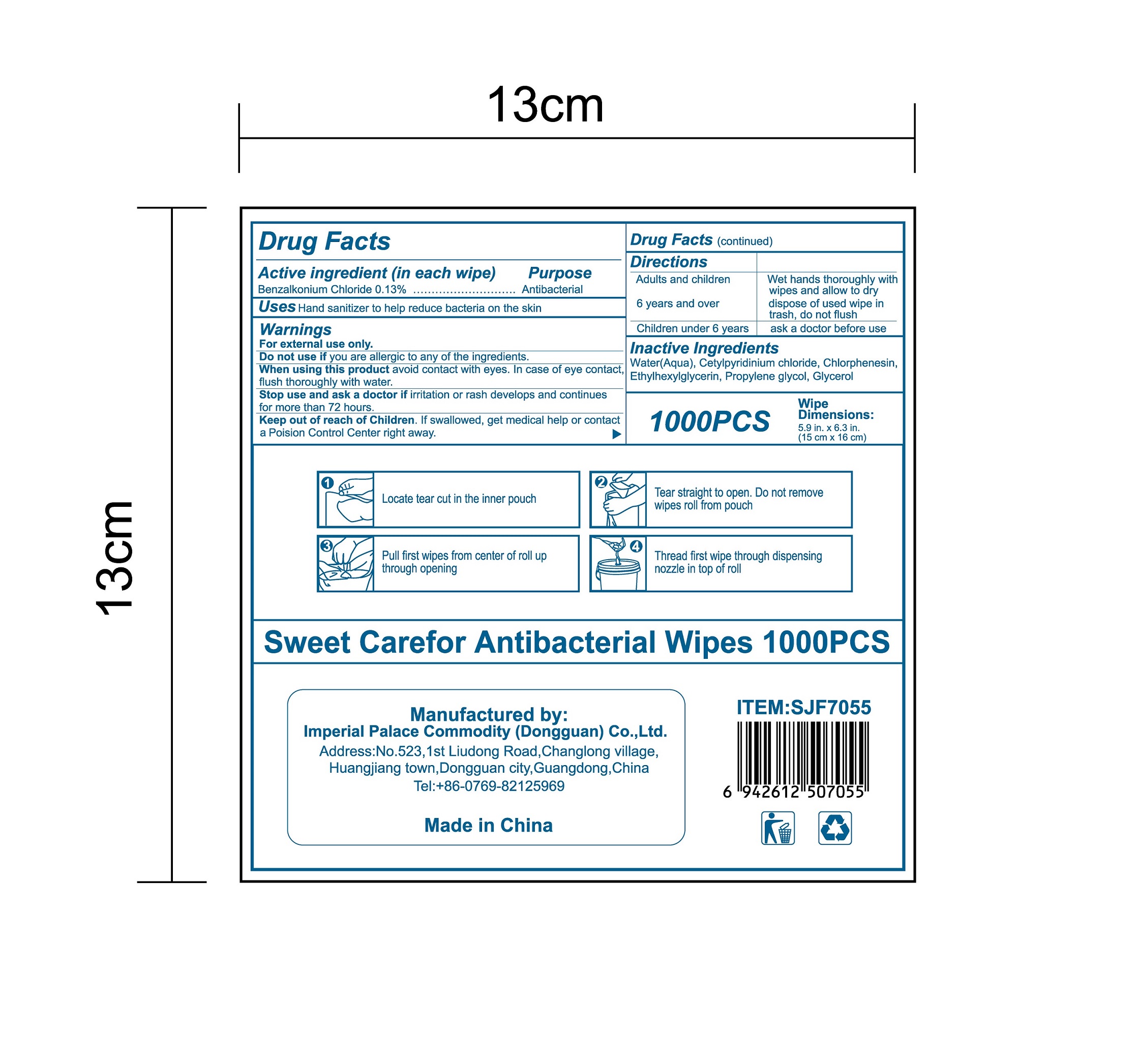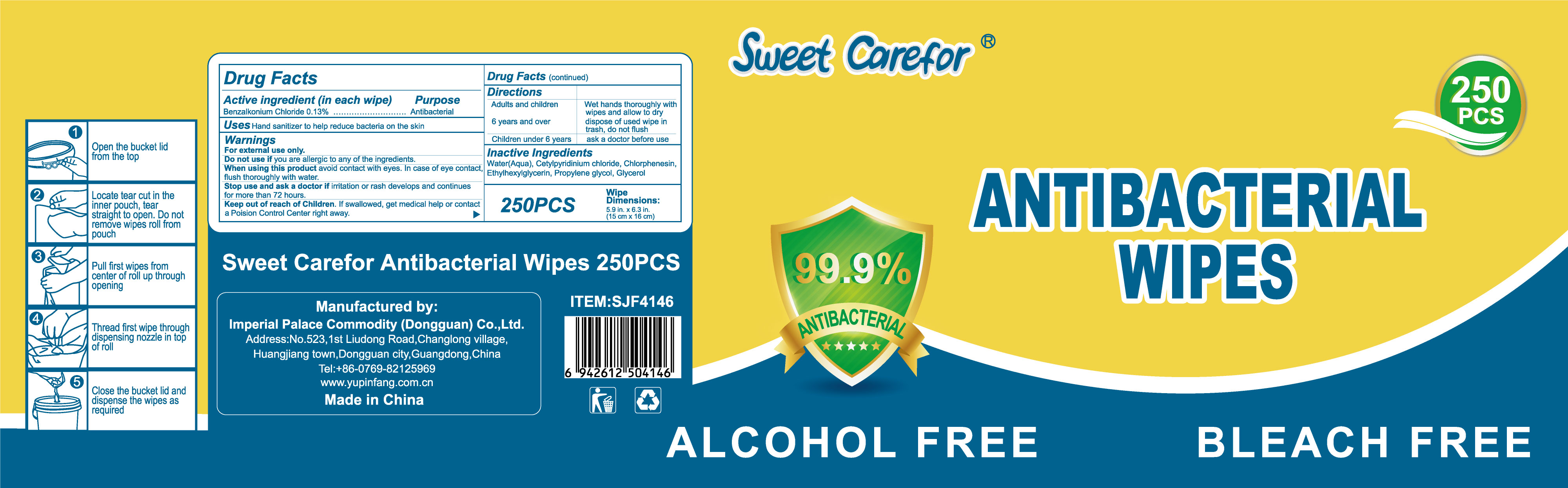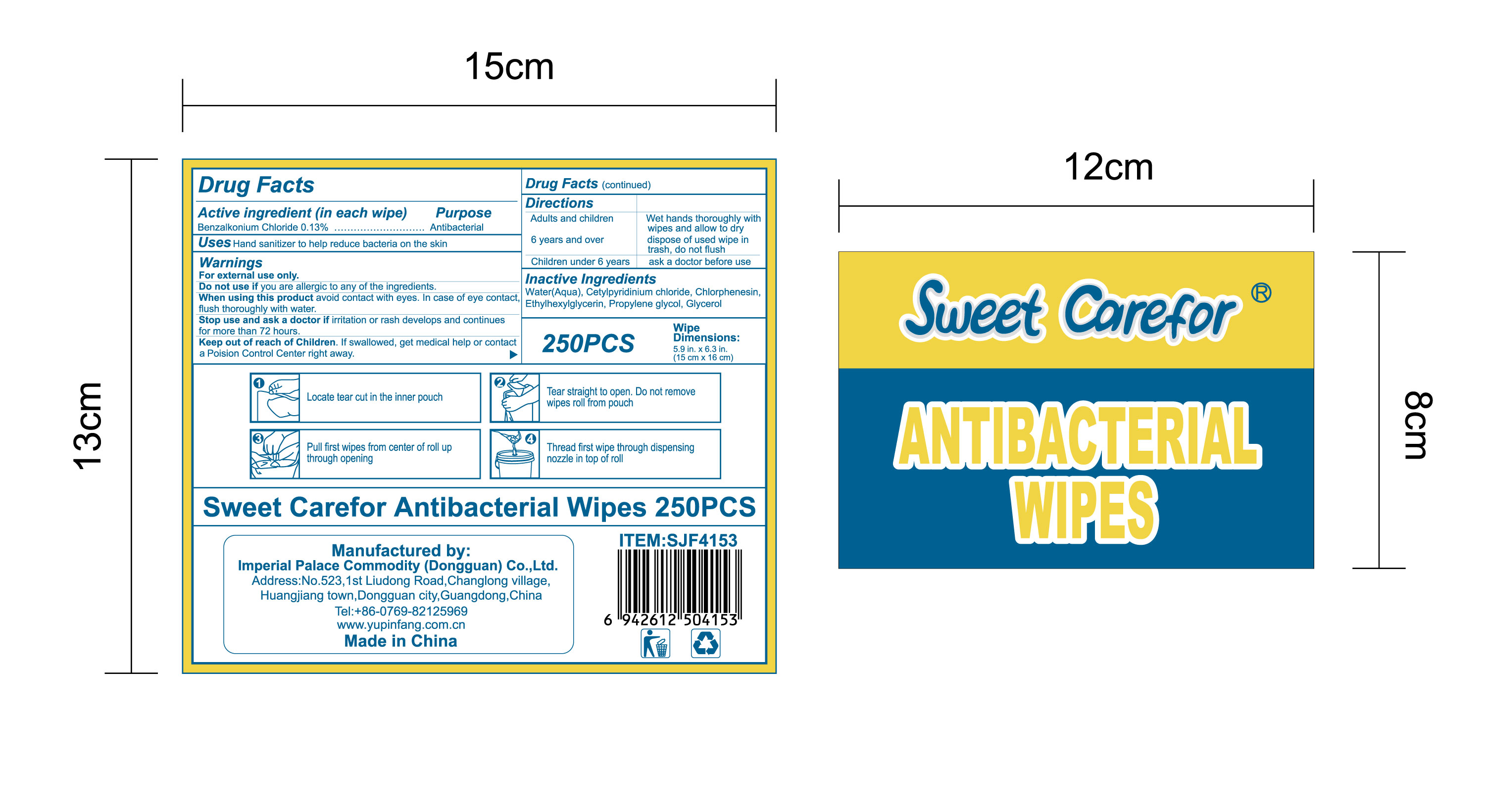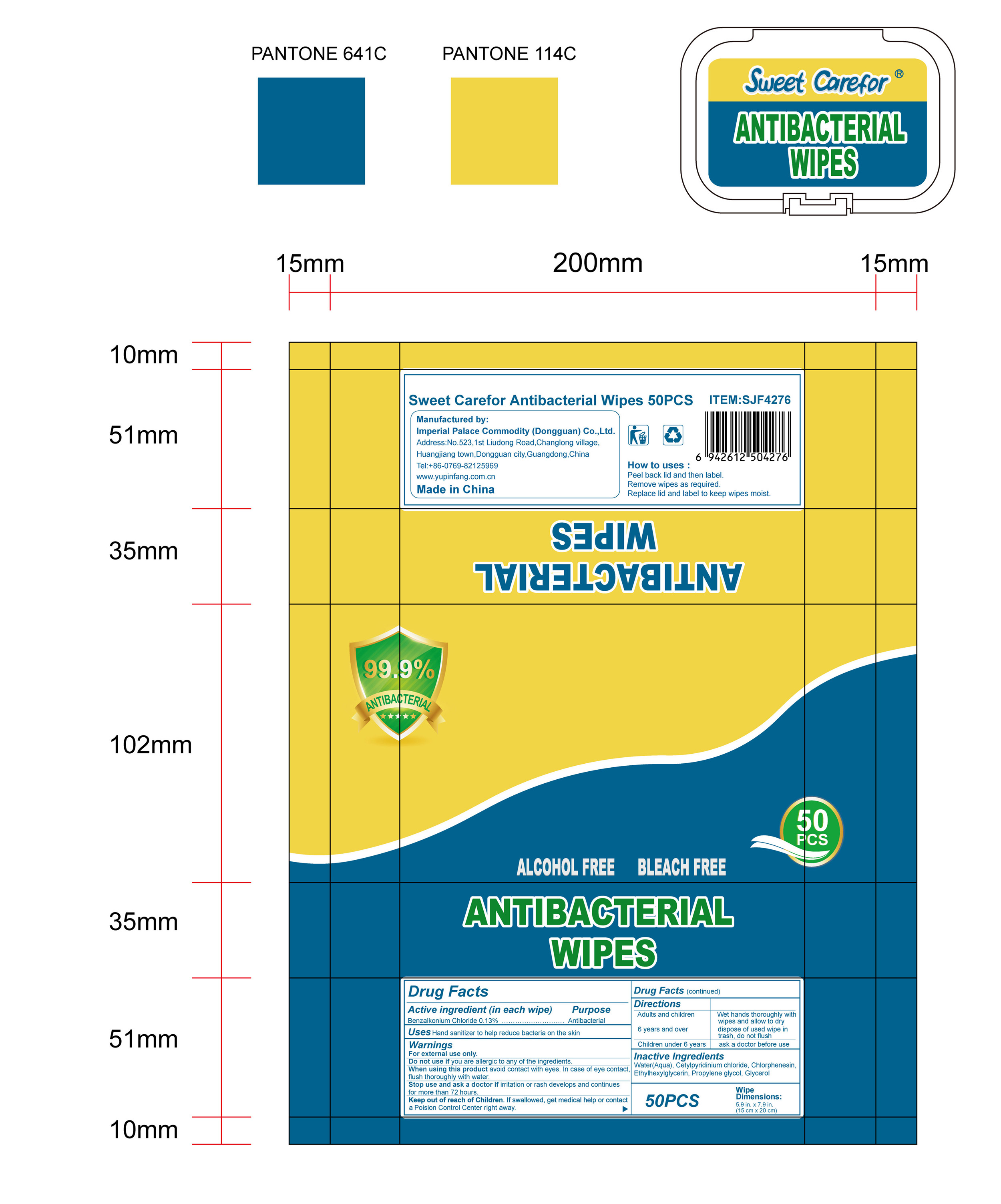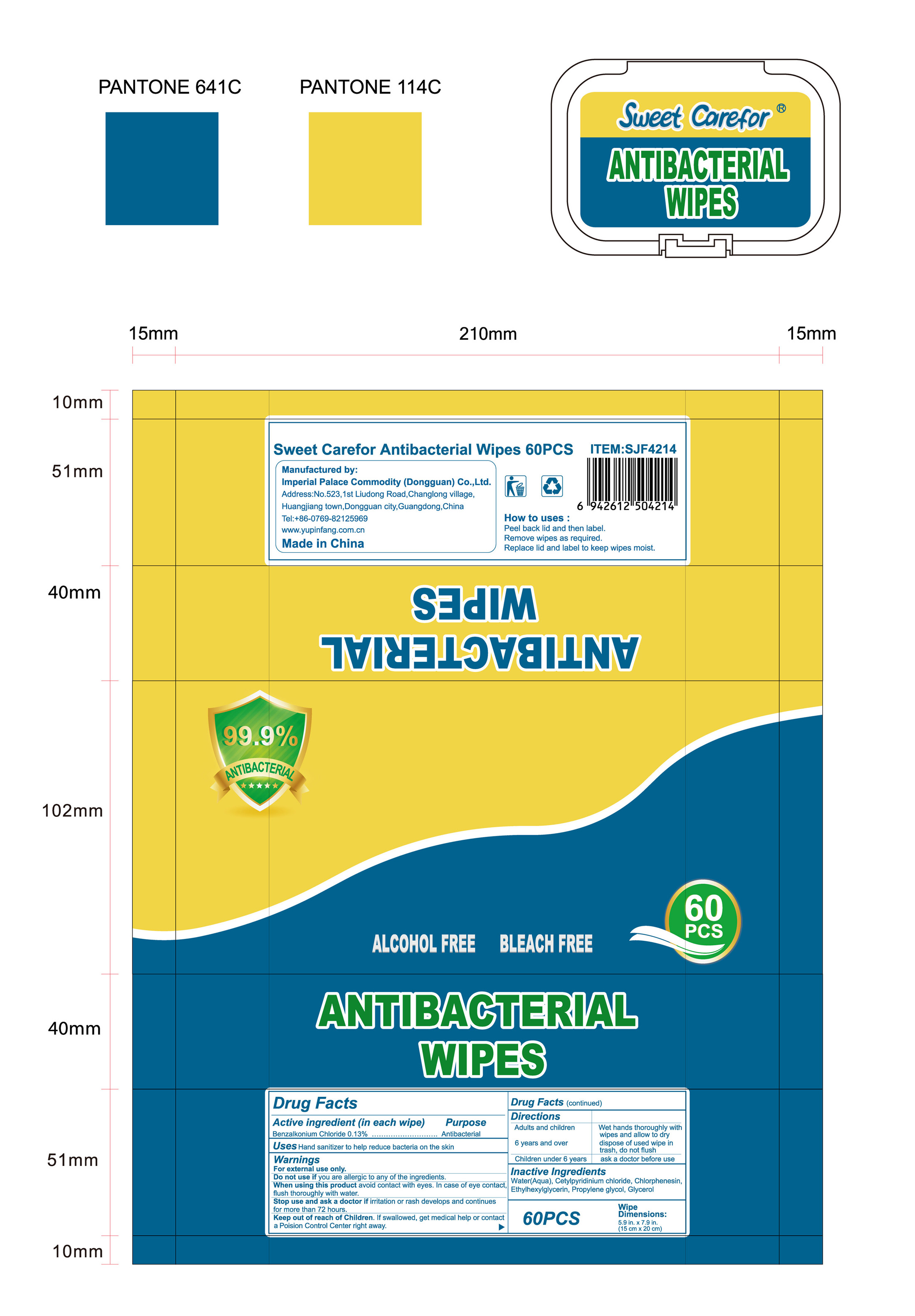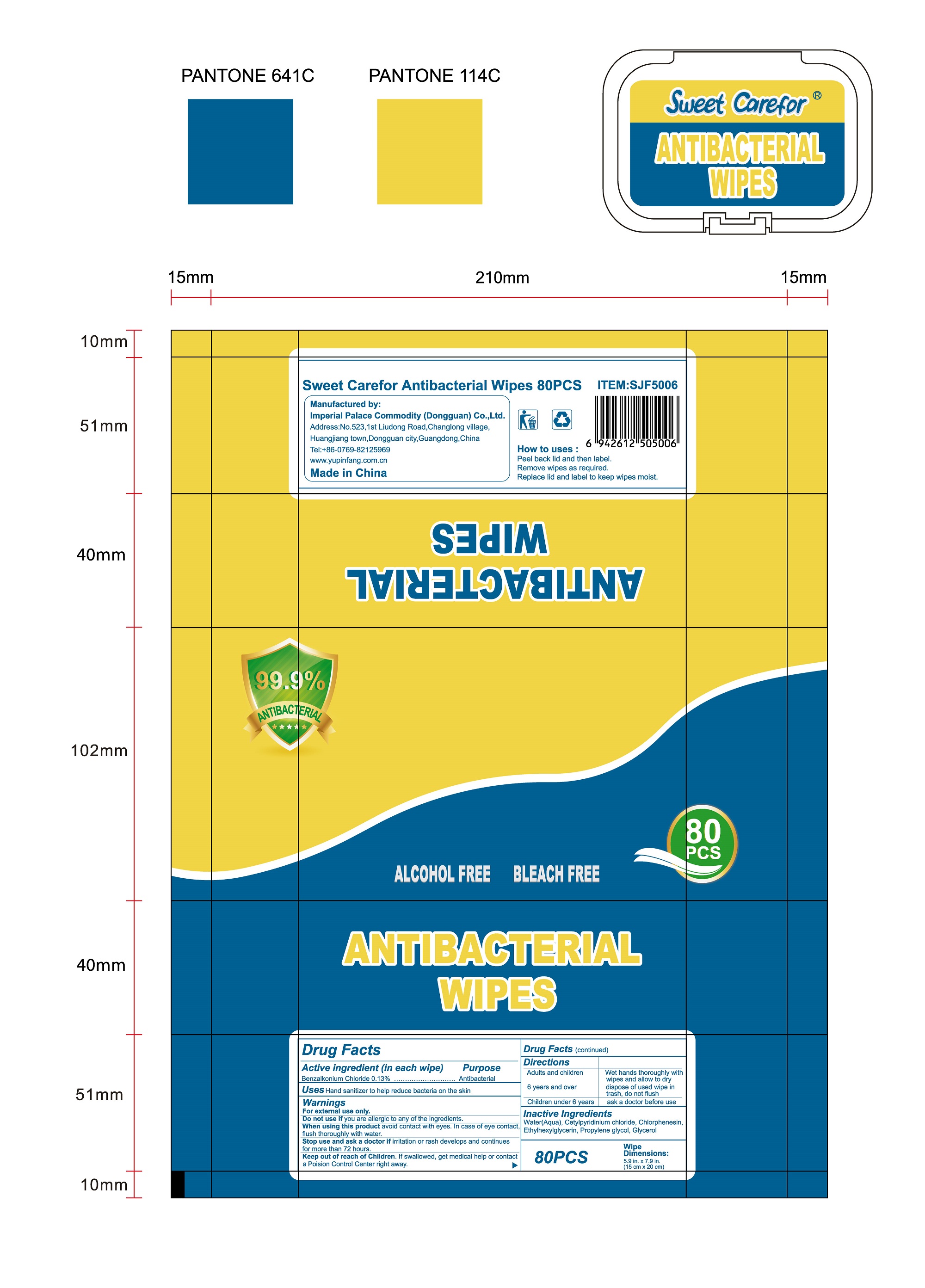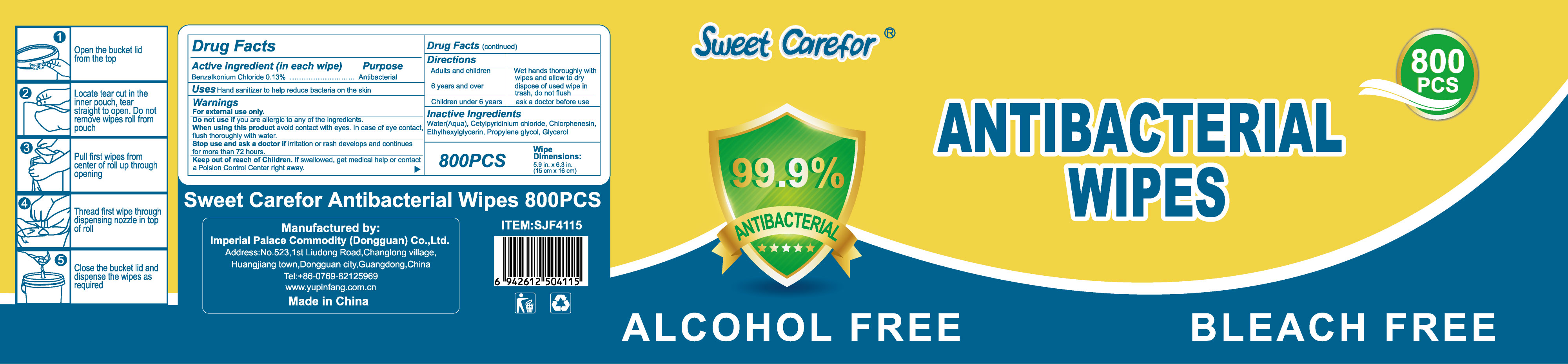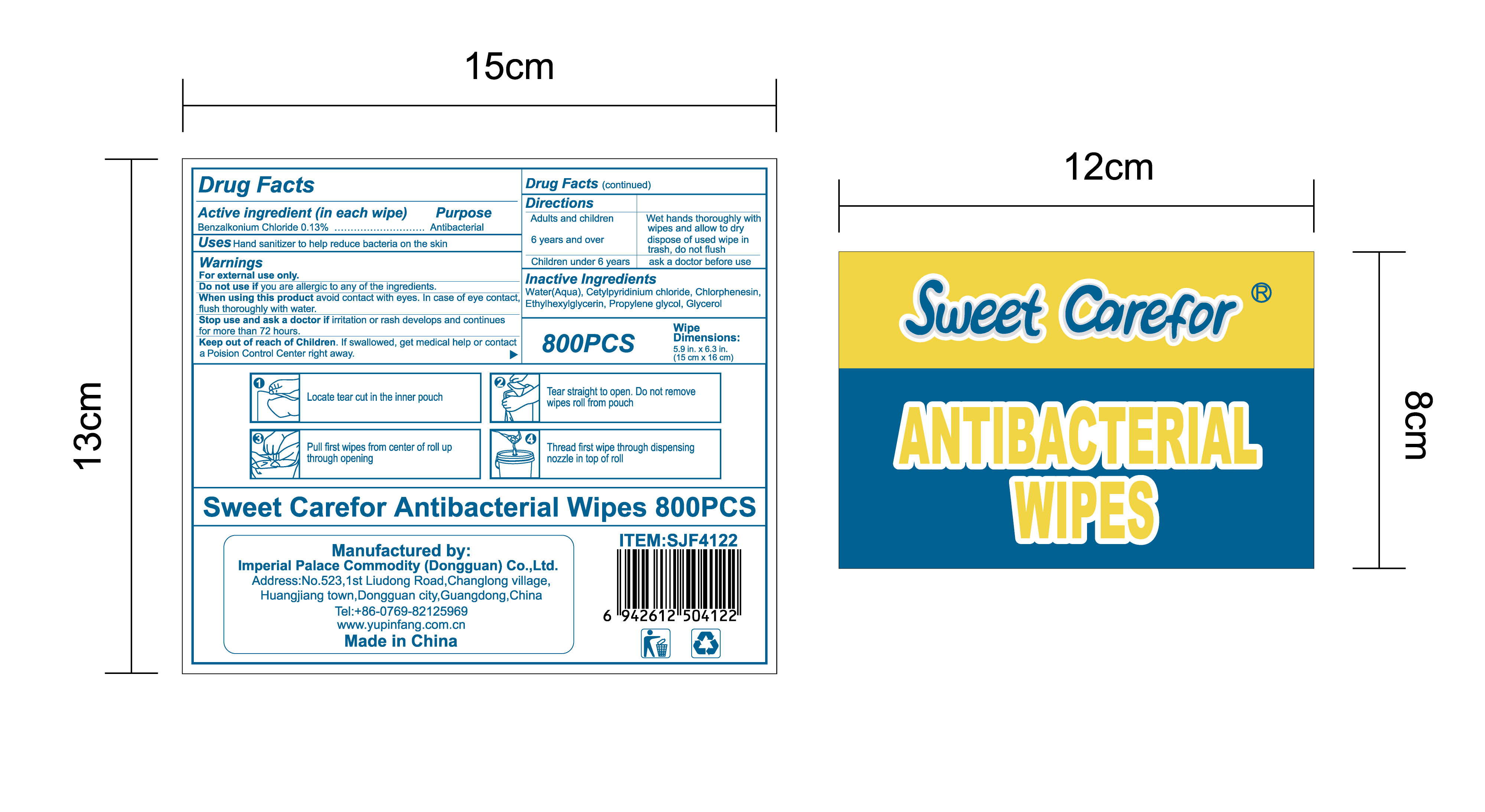 DRUG LABEL: Antibacterial Wipes
NDC: 52489-002 | Form: CLOTH
Manufacturer: Imperial Palace Commodity (shenzhen) Co., Ltd
Category: otc | Type: HUMAN OTC DRUG LABEL
Date: 20231120

ACTIVE INGREDIENTS: BENZALKONIUM CHLORIDE 1.3 mg/1 mL
INACTIVE INGREDIENTS: PROPYLENE GLYCOL; ETHYLHEXYLGLYCERIN; GLYCERIN; CETYLPYRIDINIUM CHLORIDE; WATER; CHLORPHENESIN

DRUG FACTS

Active Ingredient(s)

Benzalkonium chloride ：0.13% (W/W)

Purpose

Antibacterial

Use

Hand sanitizer to help reduce bacteria on the skin.

Warnings

For external use only.

Do not use if you are allergic to any of the ingredients.

When using this product avoid contact with eyes. In case of eye contact,flush thoroughly with water.

Stop use and ask a doctor if irritation or rash develops and continues for more than 72 hours.

Keep out of reach of Children. If swallowed, get medical help or contact a Poision Control Center right away.

Directions

Adults and children 6 years and over :

Wet hands thoroughly with wipes and allow to dry, dispose of used wipe in trash, don not flush

Children under 6 years:

ask a doctor before use.

How to uses

Packs

●Peel back lid and then label.

●Remove wipes as required.

●Replace lid and label to keep wipes moist.

Buckets

●Open the bucket lid from the top.

●Locate tear cut in the inner pouch, tear straight to open. Do not remove wipesroll from pouch.

●Pull first wipes from center of roll up through opening.

●Thread first wipe through dispensing nozzle in top of roll.

●Close the bucket lid and dispense the wipes as required.

Inactive ingredients

●Water(Aqua)

●Cetylpyridinium chloride

●Chlorphenesin

●Ethylhexylglycerin

●Propylene glycol

●Glycerol

Package Label - Principal Display Panel

NDC:52489-002-01

NDC:52489-002-02

NDC:52489-002-03

NDC:52489-002-04

NDC:52489-002-05

NDC:52489-002-06

NDC:52489-002-07

NDC:52489-002-08

NDC:52489-002-09